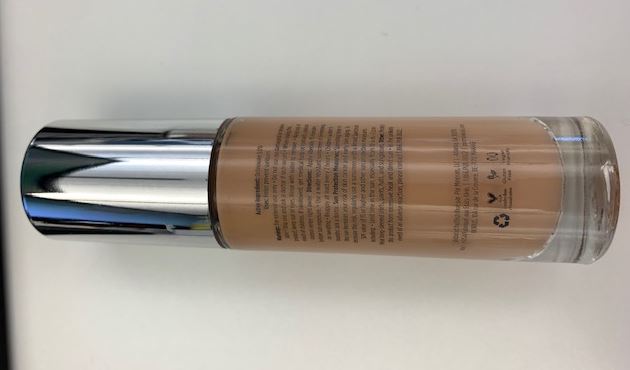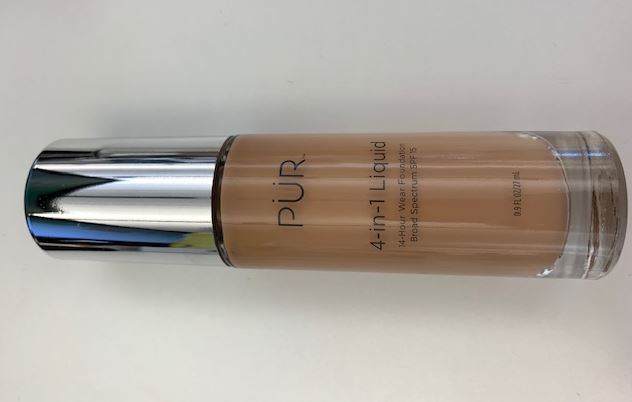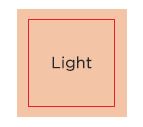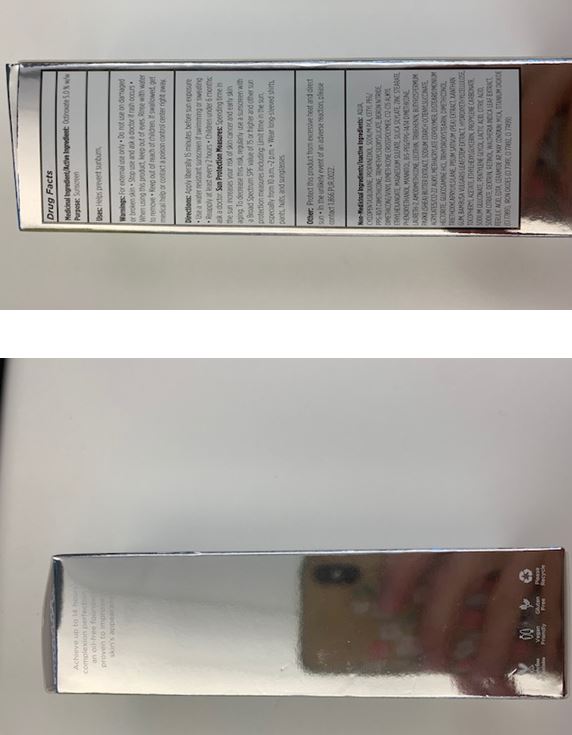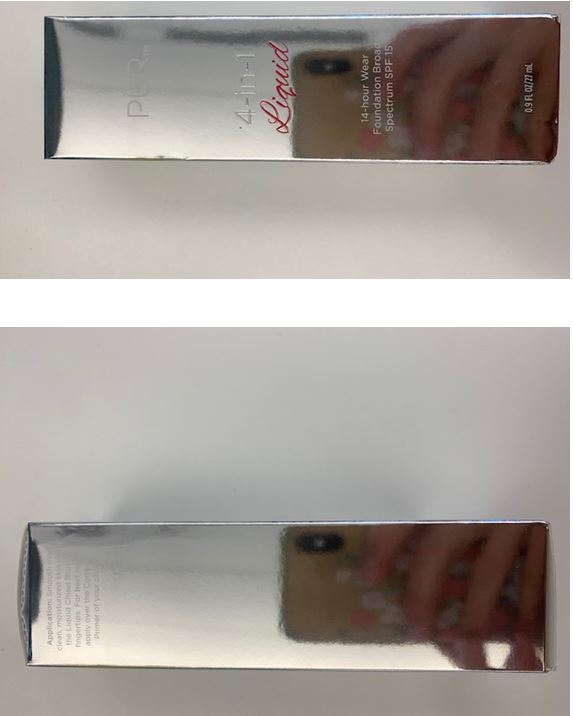 DRUG LABEL: Foundation
NDC: 61354-040 | Form: EMULSION
Manufacturer: Oxygen Development LLC
Category: otc | Type: HUMAN OTC DRUG LABEL
Date: 20230210

ACTIVE INGREDIENTS: OCTINOXATE 4.9965 mg/100 mg
INACTIVE INGREDIENTS: SILICA DIMETHYL SILYLATE; STARCH, CORN; WATER; C12-15 ALKYL ETHYLHEXANOATE; MAGNESIUM SULFATE, UNSPECIFIED FORM; TRIBEHENIN; LECITHIN, SOYBEAN; CYCLOMETHICONE 5; PROPANEDIOL; SODIUM PYRROLIDONE CARBOXYLATE; PHENOXYETHANOL; TRIMETHYLSILOXYSILICATE (M/Q 0.8-1.0); DIMETHICONE/DIVINYLDIMETHICONE/SILSESQUIOXANE CROSSPOLYMER; MANNITOL; BIS-PEG/PPG-14/14 DIMETHICONE; CETYL PEG/PPG-10/1 DIMETHICONE (HLB 2); MICA; BORON NITRIDE; ZINC STEARATE; LAURETH-7

PUR 4-IN-1 LIQUID 14-HOUR WEAR FOUNDATION BROAD SPECTRUM SPF 15 LIGHT

Medicinal Ingredient / Active Ingredient

Octinoxate 5.0% w/w

Purpose

Sunscreen

Uses

Helps prevent sunburn.

Warnings

For external use only. Do not use on damaged or broken skin. Stop use and ask a doctor if rash occurs. When using this product, keep out of eyes. Rinse with water to remove.

Keep out of reach of children. If swallowed, get medical help or contact a Poison Control Center right away.

Directions

Apply liberally 15 minutes before sun exposure. Use a water resistant sunscreen if swimming or sweating.
Reapply at least every 2 hours. Children under 6 months: ask a doctor.
Sun Protection Measures. Spending time in the sun increases your risk of skin cancer and early skin aging. To decrease this risk, regularly use a sunscreen with a Broad Spectrum SPF value of 15 or higher and other sun protection measures including:
Limit time in the sun, especially from 10am to 2 pm
Wear long-sleeved shirts, pants, hats, and sunglasses

Other

Protect this product from excessive heat and direct sun.
In the unlikely event of an adverse reaction, please contact 1.866.PUR.0022.

Non-medicinal Ingredients / Inactive Ingredients

Aqua, Cyclopentasiloxane, Propanediol, Sodium PCA, Cetyl PEG/PPG-10/1 Dimethicone,Trimethylsiloxysilicate, Boron Nitride, Dimethicone/Vinyl Dimethicone Crosspolymer, C12-15 Alkyl Ethylhexanoate, Magnesium Sulfate, Silica Silylate, Zinc Stearate, Phenoxyethanol, Mannitol, Bis-PEG/PPG-14/14 Dimethicone, Laureth-7, Amodimethicone, Lecithin, Tribehenin, Butyrospermum Parkii (Shea) Butter Extract, Sodium Starch Octenylsuccinate, Acrylates/C12-22 Alkyl Methacrylate Copolymer, Disteardimonium Hectorite, Glucosamine HCl, Trihydroxystearin, Dimethiconol, Triethoxycaprylylsilane, Pisum Sativum (Pea) Extract, Xanthan Gum, Bambusa Vulgaris Leaf/Stem Extract, Hydroxyethylcellulose, Tocopheryl Acetate, Ethylhexylglycerin, Propylene Carbonate, Sodium Gluconate, Pentylene Glycol, Lactic Acid, Citric Acid, Sodium Citrate, Dextrin, Retinol, Waltheria Indica Leaf Extract, Ferulic Acid, EDTA, Ceramide AP, May Contain: Mica, Titanium Dioxide (CI 77891), Iron Oxides (CI 77491, CI 77492, CI 77499).